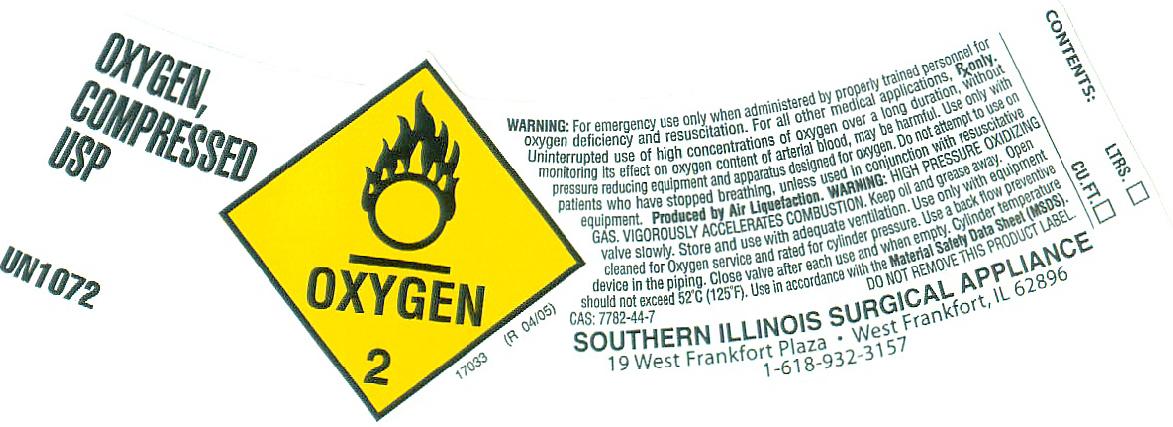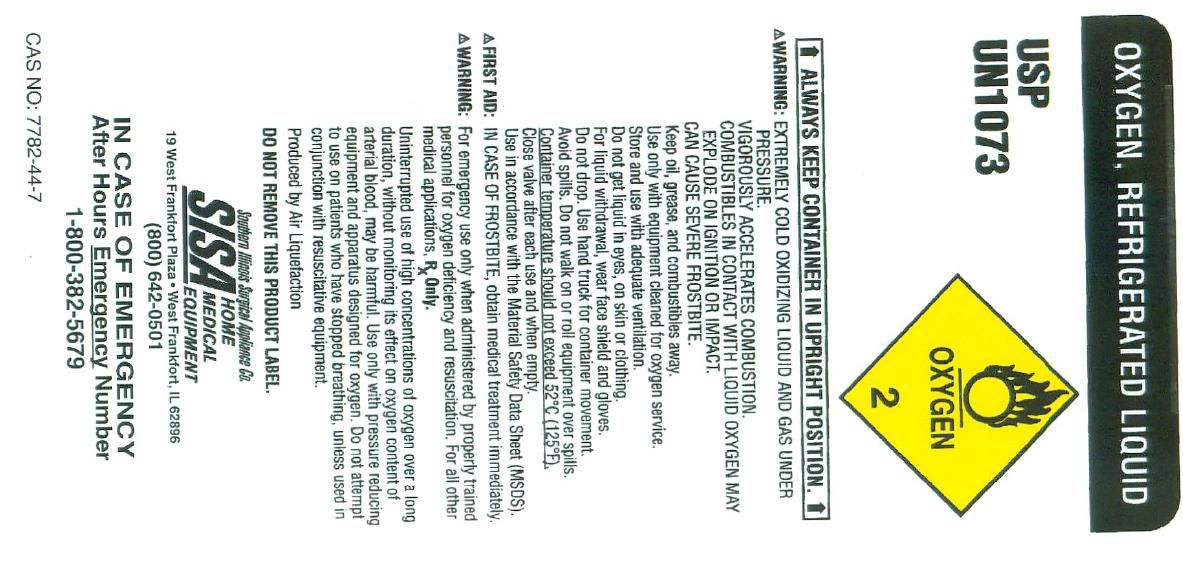 DRUG LABEL: Oxygen
NDC: 62995-001 | Form: GAS
Manufacturer: Southern ILlinois Surgical Appliance Co
Category: prescription | Type: HUMAN PRESCRIPTION DRUG LABEL
Date: 20100517

ACTIVE INGREDIENTS: Oxygen 992 mL/1 L

oxygen

PACKAGE LABEL

OXYGEN, COMPRESSED LIQUID USP UN1072 OXYGEN 2
17033 (R 04/05)
WARNING: For emergency use only when administered by properly trained personnel for oxygen deficiency and resuscitation. For all other medical applications, Rx only. Uninterrupted use of high concentrations of oxygen over a long duration, without monitoring its effect on oxygen content of arterial blood, may be harmful. Use only with pressure reducing equipment and apparatus designed for oxygen. Do not attempt to use on patients who have stopped breathing, unless used in conjunction with resuscitative equipment. Produced by Air Liquefaction.
WARNING: HIGH PRESSURE OXIDIZING GAS. VIGOROUSLY ACCELERATES COMBUSTION. Keep oil and grease away. Open valve slowly. Store and use with adequate ventilation. Use only with equipment cleaned for oxygen service and rated for cylinder pressure. Use back flow preventive device in the piping. Close valve after each use and when empty. Cylinder temperature should not exceed 52C (125F). Use in accordance with the Material Safety Data Sheets (MSDS). CAS: 7782-44-7 DO NOT REMOVE THIS PRODUCT LABEL.
SOUTHERN ILLINOIS SURGICAL APPLIANCE 19 West Frankfort Plaza West Frankfort, IL 62896 1-618-932-3157
CONTENTS: LTRS. CU. FT.

PACKAGE LABEL

OXYGEN, REFRIGERATED LIQUID U.S.P. UN1073 OXYGEN 2
ALWAYS KEEP CONTAINER IN UPRIGHT POSITION
WARNING: EXTREMELY COLD, OXIDIZING LIQUID AND GAS UNDER PRESSURE. VIGOROUSLY ACCELERATES COMBUSTION. COMBUSTIBLES IN CONTACT WITH LIQUID OXYGEN MAY EXPLODE ON IGNITION OR IMPACT. CAN CAUSE SEVERE FROSTBITE. Keep oil, grease, and combustibles away. Use only with equipment cleaned for oxygen service. Store and use with adequate ventilation. Do not get liquid in eyes, on skin, or clothing. For liquid withdrawal, wear face shield and gloves. Do not drop. Use suitable hand truck for container movement. Avoid spills. Do not walk on or roll equipment over spills. Container temperature should not exceed 52C (125F). Close valve after each use and when empty. Use in accordance with the Material Safety Data Sheet (MSDS). FIRST AID: IN CASE OF FROSTBITE, obtain medical treatment immediately.
WARNING: For emergency use only when administered by properly trained personnel for oxygen deficiency and resuscitation. For all other medical applications, Rx Only.
Uninterrupted use of high concentrations of oxygen over a long duration, without monitoring its effect on oxygen content of arterial blood, may be harmful. Use only with pressure reducing equipment and apparatus designed for oxygen. Do not attempt to use on patients who have stopped breathing, unless used in conjunction with resuscitative equipment.
Produced by Air Liquefaction.
DO NOT REMOVE THIS PRODUCT LABEL.
Southern Illinois Surgical Appliance Co.
SISA HOME MEDICAL EQUIPMENT 19 West Frankfort Plaza West Frankfort, IL 62896 (800) 642- 0501 IN CASE OF EMERGENCY After Hours Emergency Number 1-800-382-5679
CAS NO: 7782-44-7